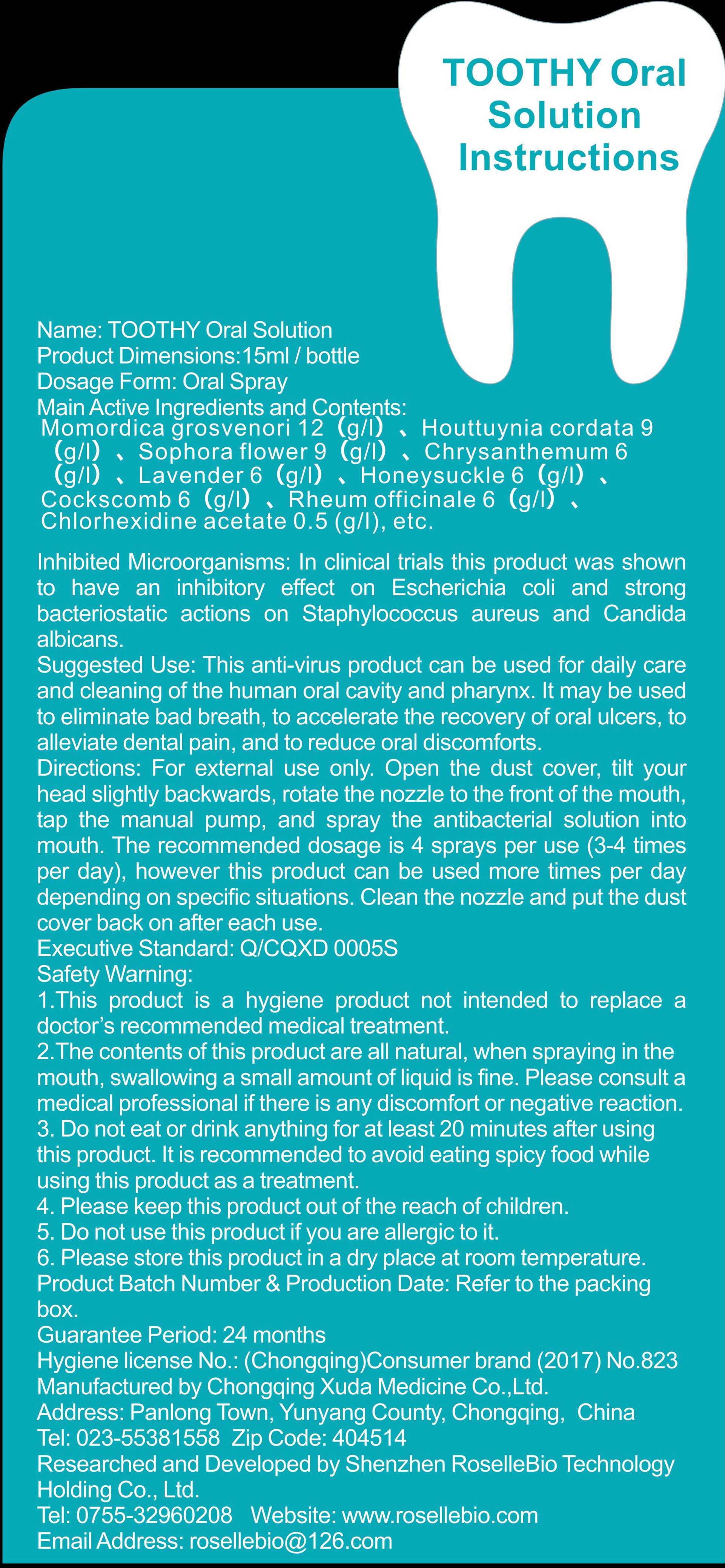 DRUG LABEL: Toothy Oral Solution
NDC: 54465-001 | Form: LIQUID
Manufacturer: Shenzhen Roselle Bio-Technology Holding Co.,Ltd.
Category: otc | Type: HUMAN OTC DRUG LABEL
Date: 20200415

ACTIVE INGREDIENTS: SOPHORA FLAVESCENS WHOLE 135 g/15 L; HOUTTUYNIA CORDATA WHOLE 135 g/15 L
INACTIVE INGREDIENTS: ERIASTRUM FILIFOLIUM WHOLE; CHRYSANTHEMIC ACID, (+/-)-; LONICERA CONFUSA FLOWER; SIRAITIA GROSVENORII FRUIT; CELOSIA CRISTATA WHOLE; RHEUM OFFICINALE WHOLE; CHLORHEXIDINE ACETATE

DOSAGE AND ADMINISTRATION

Please store this product in a dry place at room temperature.

INACTIVE INGREDIENT

Momordica grosvenori

Chrysanthemum

Lavender

Honeysuckle

Cockscomb

Rheum officinale

Chlorhexidine acetate

INDICATIONS AND USAGE

For external use only. Open the dust cover, tilt your head slightly backwards, rotate the nozzle to the front of the mouth,tap the manual pump, and spray the antibacterial solution into mouth. The recommended dosage is 4 sprays per use (3-4 times per day), however this product can be used more times per day depending on specific situations. Clean the nozzle and put the dust cover back on after each use.

ACTIVE INGREDIENT

Sophora flower

Houttuynia cordata

keep out of children

PURPOSE

Disinfection
Sterilization

WARNINGS

1.This product is a hygiene product not intended to replace a doctor' S recommended medical treatment.
2.The contents of this product are all natural, when spraying in the mouth, swallowing a small amount of liquid is fine. Please consult a
medical professional if there is any discomfort or negative reaction.
3. Do not eat or drink anything for at least 20 minutes after using this product. It is recommended to avoid eating spicy food while using this product as a treatment.
4. Please keep this product out of the reach of children.
5. Do not use this product if you are allergic to it.
6. Please store this product in a dry place at room temperature.